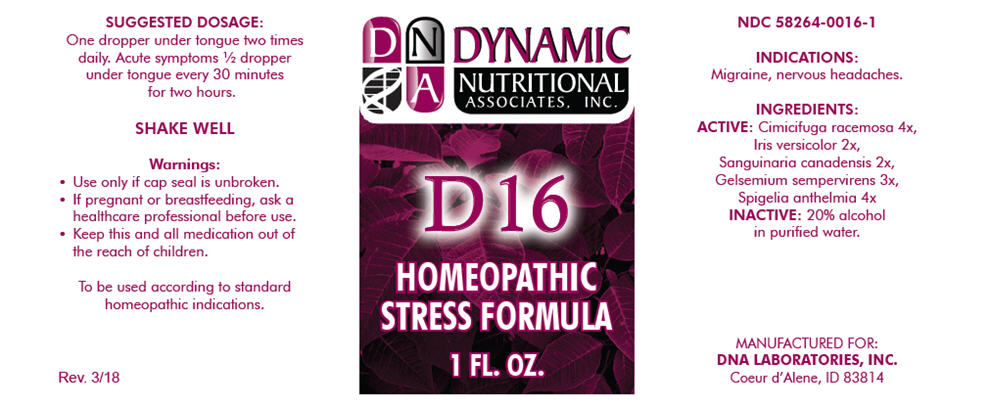 DRUG LABEL: D-16
NDC: 58264-0016 | Form: SOLUTION/ DROPS
Manufacturer: DNA Labs, Inc.
Category: homeopathic | Type: HUMAN OTC DRUG LABEL
Date: 20250113

ACTIVE INGREDIENTS: BLACK COHOSH 4 [hp_X]/1 mL; IRIS VERSICOLOR ROOT 2 [hp_X]/1 mL; SANGUINARIA CANADENSIS ROOT 2 [hp_X]/1 mL; GELSEMIUM SEMPERVIRENS ROOT 3 [hp_X]/1 mL; SPIGELIA ANTHELMIA 4 [hp_X]/1 mL
INACTIVE INGREDIENTS: ALCOHOL; WATER

D-16

NDC 58264-0016-1

INDICATIONS

PURPOSE

Migraine, nervous headaches.

INGREDIENTS

ACTIVE

Cimicifuga racemosa 4x, Iris versicolor 2x, Sanguinaria canadensis 2x, Gelsemium sempervirens 3x, Spigelia anthelmia 4x

INACTIVE

20% alcohol in purified water.

SUGGESTED DOSAGE

One dropper under tongue two times daily. Acute symptoms ½ dropper under tongue every 30 minutes for two hours.

STORAGE AND HANDLING

SHAKE WELL

Warnings

- Use only if cap seal is unbroken.

PREGNANCY OR BREAST FEEDING

- If pregnant or breastfeeding, ask a healthcare professional before use.

KEEP OUT OF REACH OF CHILDREN

- Keep this and all medication out of the reach of children.

To be used according to standard homeopathic indications.

PRINCIPAL DISPLAY PANEL - 1 FL. OZ. Bottle Label

DYNAMIC
NUTRITIONAL
ASSOCIATES, INC.

D 16

HOMEOPATHIC
STRESS FORMULA

1 FL. OZ.